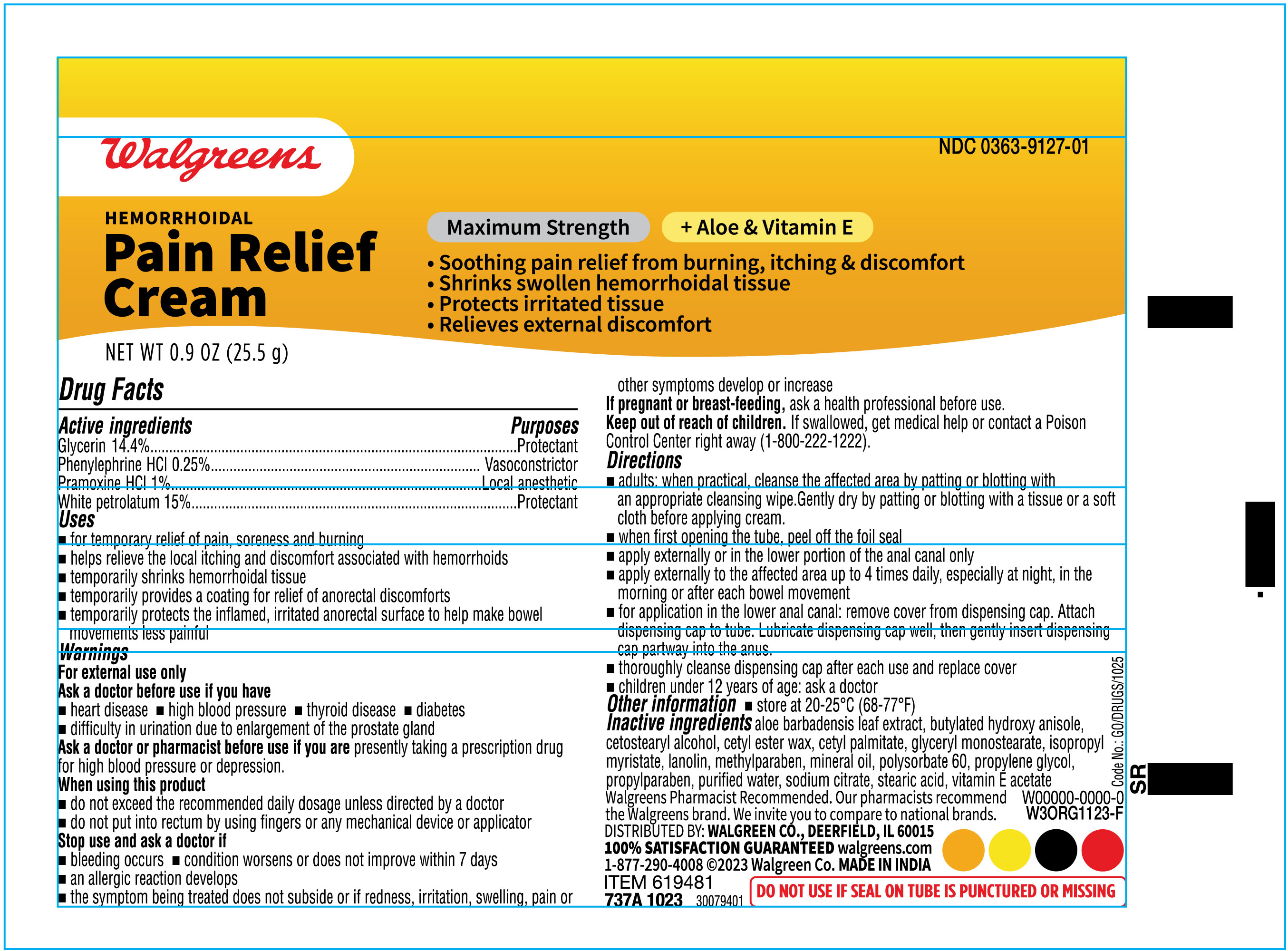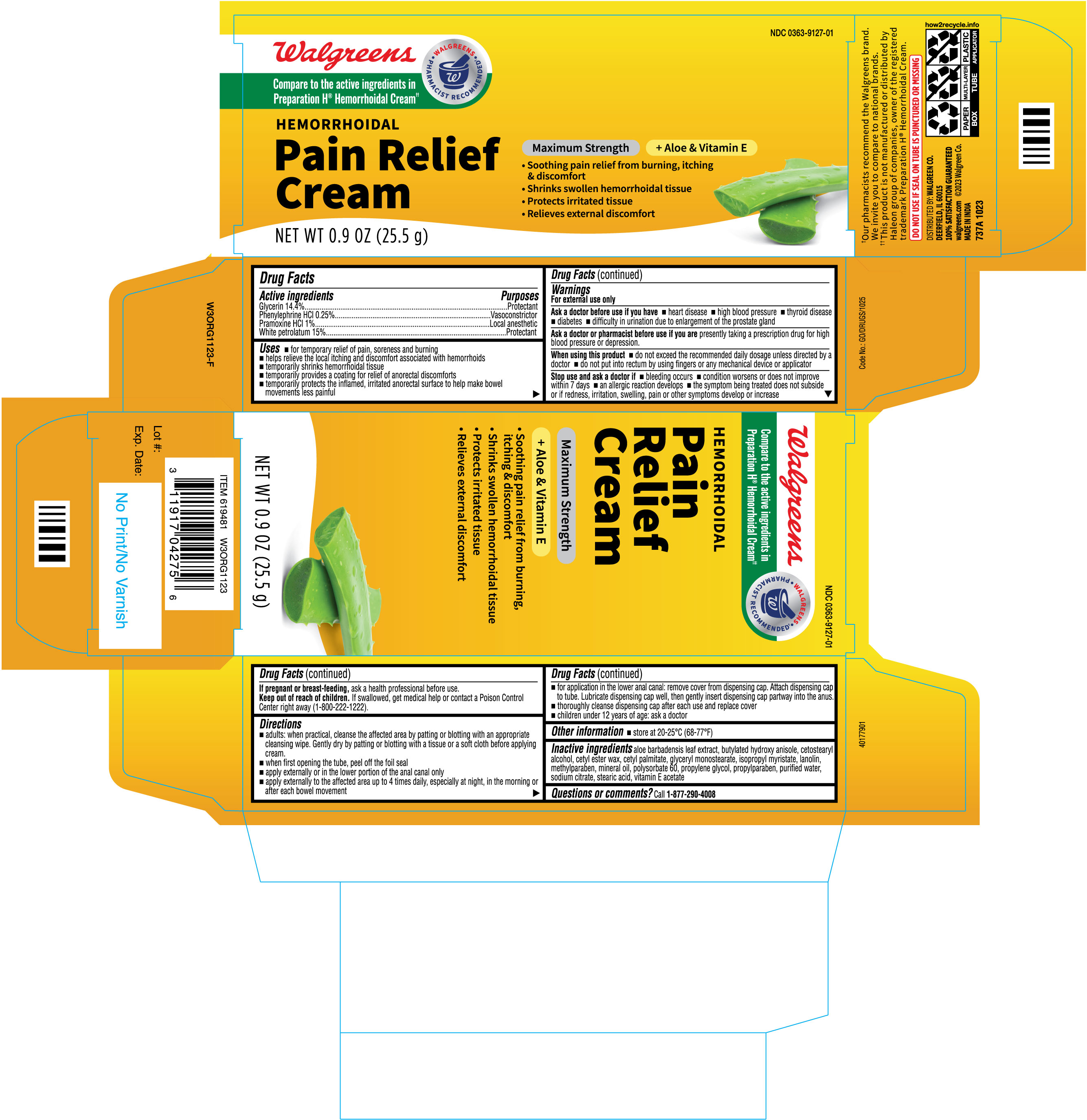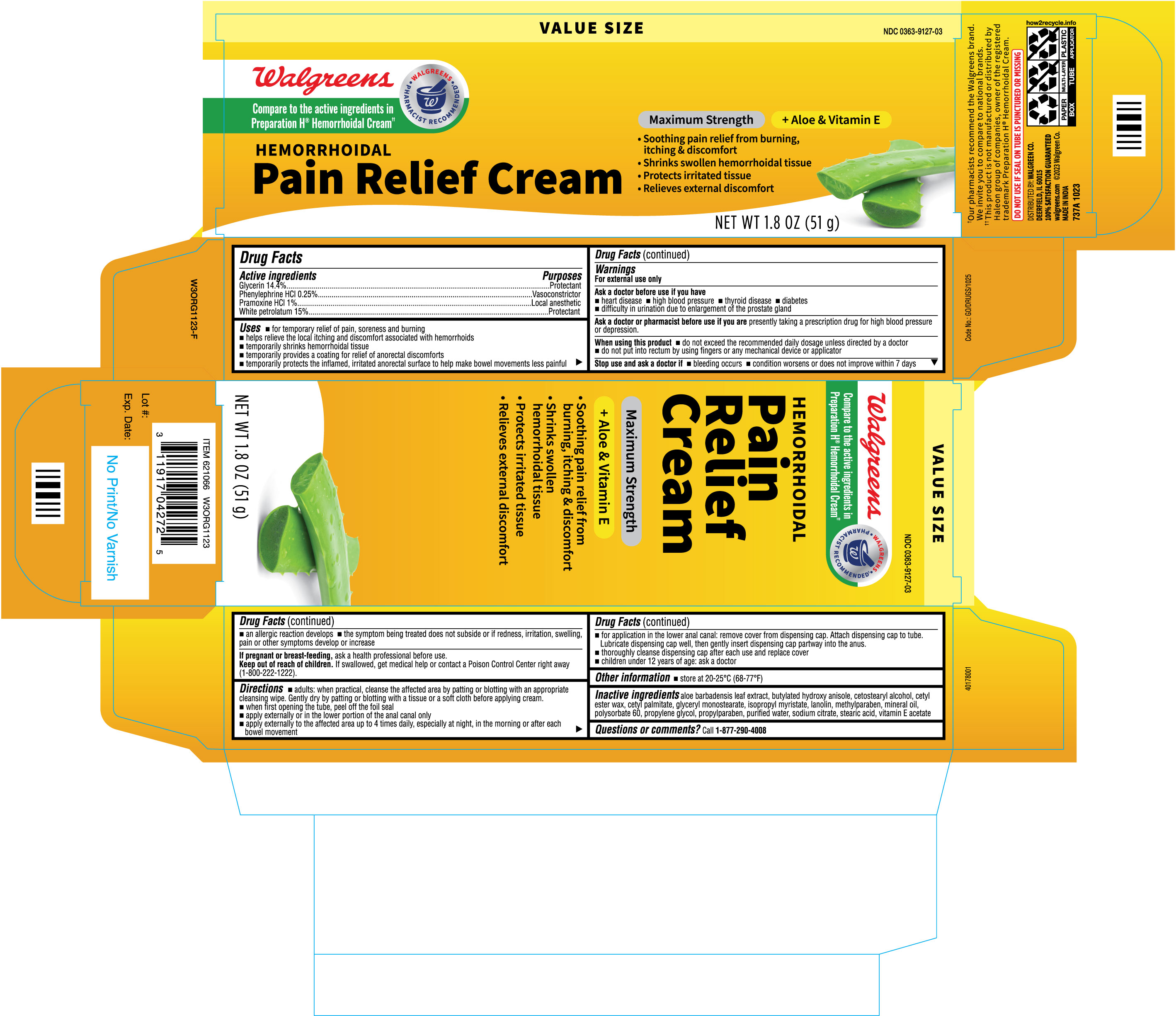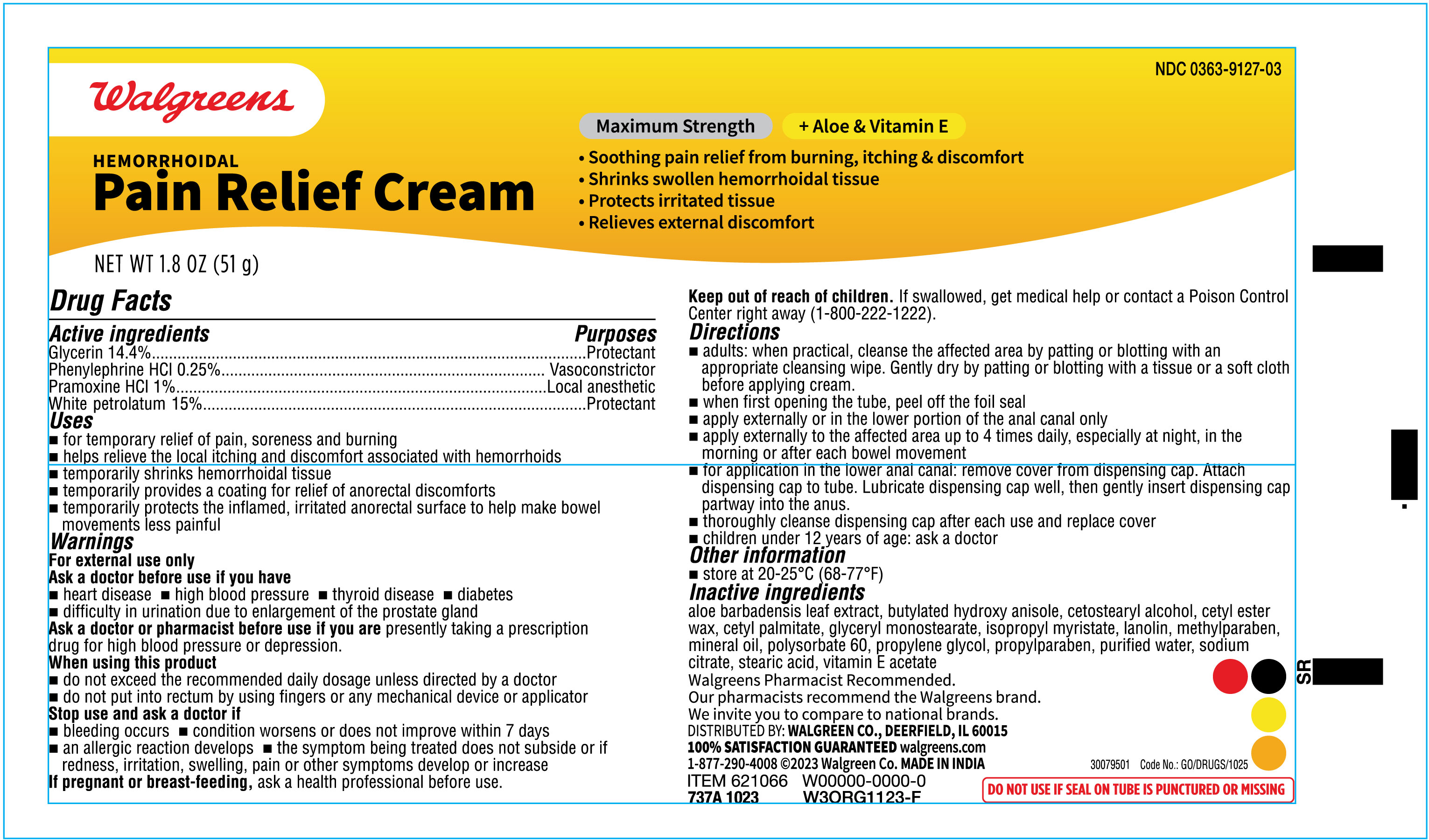 DRUG LABEL: Hemorrhoidal Pain Relief Cream
NDC: 0363-9127 | Form: CREAM
Manufacturer: WALGREENS
Category: otc | Type: HUMAN OTC DRUG LABEL
Date: 20231204

ACTIVE INGREDIENTS: GLYCERIN 144 mg/1 g; PHENYLEPHRINE HYDROCHLORIDE 2.5 mg/1 g; PRAMOXINE HYDROCHLORIDE 10 mg/1 g; PETROLATUM 150 mg/1 g
INACTIVE INGREDIENTS: GLYCERYL MONOSTEARATE; LANOLIN; MINERAL OIL; WATER; STEARIC ACID; CETYL ESTERS WAX; PROPYLPARABEN; METHYLPARABEN; CETOSTEARYL ALCOHOL; BUTYLATED HYDROXYANISOLE; ALOE VERA LEAF; PROPYLENE GLYCOL; CETYL PALMITATE; POLYSORBATE 60; ISOPROPYL MYRISTATE; ALPHA-TOCOPHEROL ACETATE; SODIUM CITRATE

Walgreens Hemorrhoidal Cream

Active ingredients
Glycerin 14.4%
Phenylephrine HCl 0.25%
Pramoxine HCl 1%
White petrolatum 15%

Purposes
Protectant
Vasoconstrictor
Local anesthetic
Protectant

Uses
• for temporary relief of pain, soreness and burning
• helps relieve the local itching and discomfort associated with hemorrhoids
• temporarily shrinks hemorrhoidal tissue
• temporarily provides a coating for relief of anorectal discomforts
• temporarily protects the inflamed, irritated anorectal surface to help make bowel movements less painful

Warnings

For external use only

Ask a doctor before use if you have

- heart disease
- high blood pressure
- thyroid disease
- diabetes
- difficulty in urination due to enlargement of the prostate gland

Ask a doctor or pharmacist before use if you are presently taking a prescription drug for high blood pressure or depression.

When using this product

- do not exceed the recommended daily dosage unless directed by a doctor
- do not put into rectum by using fingers or any mechanical device or applicator

Stop use and ask a doctor if

- bleeding occurs
- condition worsens or does not improve within 7 days
- an allergic reaction develops
- the symptom being treated does not subside or if redness, irritation, swelling, pain or
- other symptoms develop or increase

PREGNANCY OR BREAST FEEDING

If pregnant or breast-feeding, ask a health professional before use.

Keep out of reach of children. If swallowed, get medical help or contact a Poison Control Center right away (1-800-222-1222).

Directions

- adults: when practical, cleanse the affected area by patting or blotting with an appropriate cleansing wipe. Gently dry by patting or blotting with a tissue or a soft cloth before applying cream.
- when first opening the tube, peel off the foil seal
- apply externally or in the lower portion of the anal canal only
- apply externally to the affected area up to 4 times daily, especially at night, in the morning or after each bowel movement
- for application in the lower anal canal: remove cover from dispensing cap. Attach dispensing cap to tube. Lubricate dispensing cap well, then gently insert dispensing cap partway into the anus.
- thoroughly cleanse dispensing cap after each use and replace cover
- children under 12 years of age: ask a doctor

Other information

- store at 20-25 °C (68-77 °F)

INACTIVE INGREDIENT

Inactive ingredients aloe barbadensis leaf extract, butylated hydroxy anisole, cetostearyl alcohol, cetyl ester wax, cetyl palmitate, glyceryl monostearate, isopropyl myristate, lanolin, methylparaben, mineral oil, polysorbate 60, propylene glycol, propylparaben, purified water, sodium citrate, stearic acid, vitamin E acetate

Questions or comments?

Call 1-877-290-4008